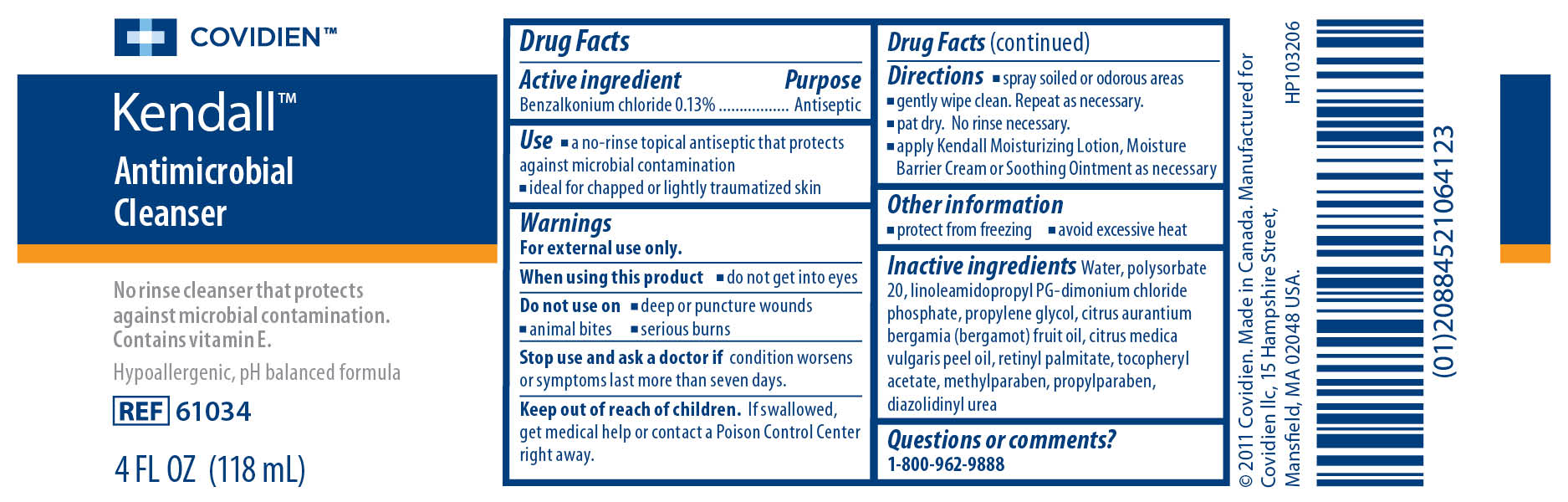 DRUG LABEL: Kendall Antimicrobial Cleanser
NDC: 28851-691 | Form: LIQUID
Manufacturer: Covidien Inc.
Category: otc | Type: HUMAN OTC DRUG LABEL
Date: 20110405

ACTIVE INGREDIENTS: Benzalkonium Chloride 0.13 mL/100 mL
INACTIVE INGREDIENTS: Water; POLYSORBATE 20; PHOSPHATE ION; PROPYLENE GLYCOL ; BERGAMOT OIL ; VITAMIN A PALMITATE; ACETATE ION; METHYLPARABEN; PROPYLPARABEN ; DIAZOLIDINYL UREA

Kendall Antimicrobial Cleanser

Active Ingredient

Benzalkonium Chloride 0.13%

Purpose

Antiseptic

Use

- a no-rinse topical antiseptic that protects against microbial contamination
- ideal for chapped or lightly traumatized skin

Warnings

For external use only.
When using this product

- do not get into eyes

Do not use on

- deep or puncture wounds
- animal bites
- serious burns

Stop use and ask a doctor if condition worsens or symptoms last more than seven days.
Keep out of the reach of children. If swallowed, get medical help or contact a Poison Control Center right away.

Directions

- spray soiled or odorous areas
- gently wipe clean. Repeat as necessary.
- pat dry. No rinse necessary.
- apply Kendall Moisturizing Lotion, Moisture Barrier Cream or Soothing Ointment as necessary

Other Information

- protect from freezing
- avoid excessive heat

Inactive ingredients

Water, Polysorbate 20, linoleamidopropyl PG-dimonium chloride phosphate, propylene glycol, cirtus aurantium bergamia (bergamot) fruit oil, citrus medica vulgaris peel oil, retinyl palmitate, tocopheryl acetate, methylparaben, propylparaben, diazolidinyl urea

Questions or comments? 1-800-962-9888

Image of 4 Ounce Label